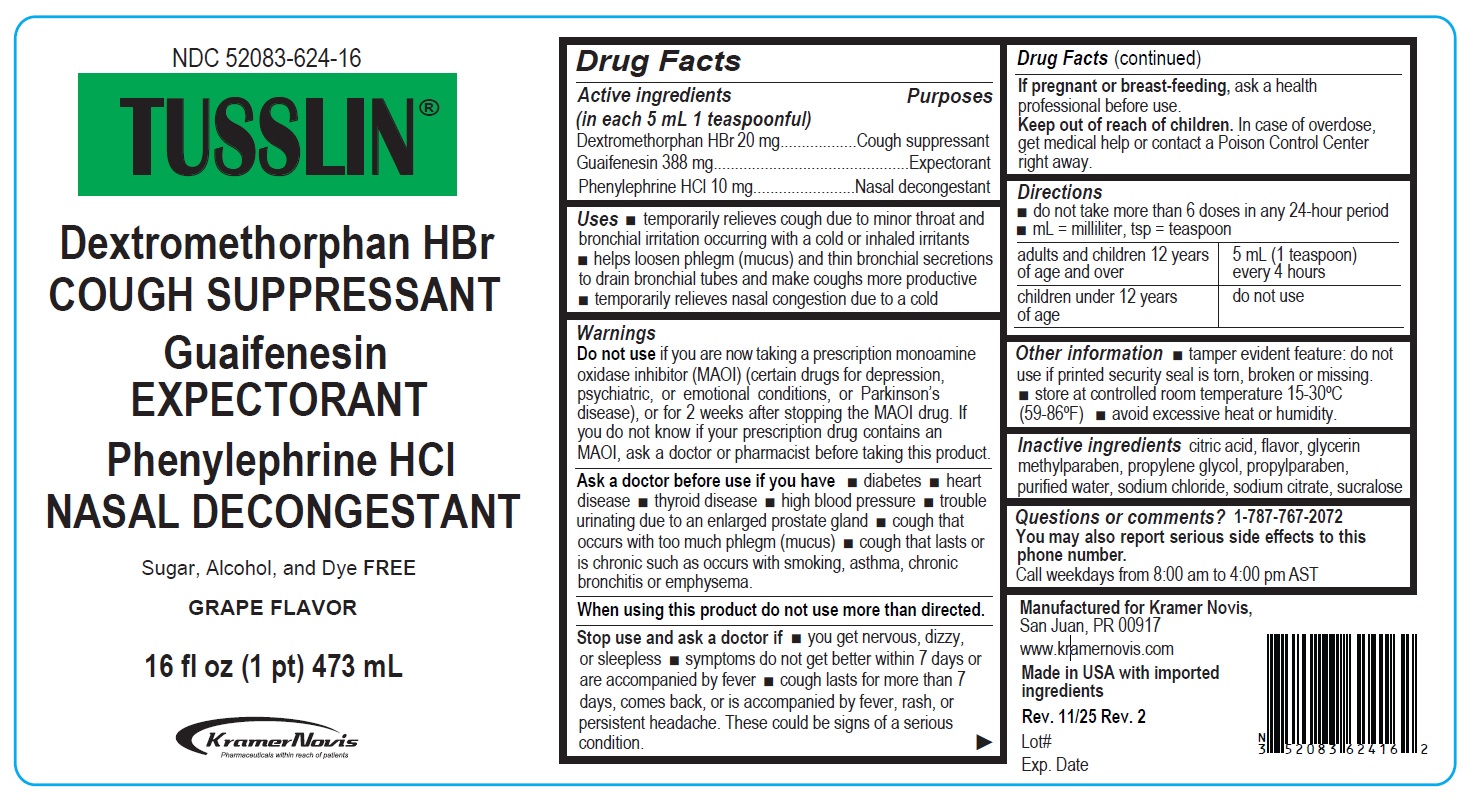 DRUG LABEL: TUSSLIN
NDC: 52083-624 | Form: SYRUP
Manufacturer: Kramer Novis
Category: otc | Type: HUMAN OTC DRUG LABEL
Date: 20251203

ACTIVE INGREDIENTS: DEXTROMETHORPHAN HYDROBROMIDE 20 mg/5 mL; GUAIFENESIN 388 mg/5 mL; PHENYLEPHRINE HYDROCHLORIDE 10 mg/5 mL
INACTIVE INGREDIENTS: CITRIC ACID MONOHYDRATE; GLYCERIN; METHYLPARABEN; PROPYLENE GLYCOL; PROPYLPARABEN; WATER; SODIUM CHLORIDE; SODIUM CITRATE, UNSPECIFIED FORM; SUCRALOSE

TUSSLIN®

Active ingredients (in each 5 mL 1 teaspoonful)

Dextromethorphan HBr 20 mg
Guaifenesin 388 mg
Phenylephrine HCl 10 mg

Purpose

Cough suppressant
Expectorant
Nasal decongestant

Uses

• temporarily relieves cough due to minor throat and bronchial irritation occurring with a cold or inhaled irritants
• helps loosen phlegm (mucus) and thin bronchial secretions to drain bronchial tubes and make coughs more productive
• temporarily relieves nasal congestion due to a cold

Warnings

Do not use if you are now taking a prescription monoamine oxidase inhibitor (MAOI) (certain drugs for depression, psychiatric, or emotional conditions, or Parkinson’s disease), or for 2 weeks after stopping the MAOI drug. If you do not know if your prescription drug contains an MAOI, ask a doctor or pharmacist before taking this product.

Ask a doctor before use if you have • diabetes • heart disease • thyroid disease • high blood pressure • trouble urinating due to an enlarged prostate gland • cough that occurs with too much phlegm (mucus) • cough that lasts or is chronic such as occurs with smoking, asthma, chronic
bronchitis or emphysema.

When using this product do not use more than directed.

Stop use and ask a doctor if • you get nervous, dizzy, or sleepless • symptoms do not get better within 7 days or are accompanied by fever • cough lasts for more than 7 days, comes back, or is accompanied by fever, rash, or persistent headache. These could be signs of a serious condition.

If pregnant or breast-feeding, ask a health professional before use.

Keep out of reach of children. In case of overdose, get medical help or contact a Poison Control Center right away.

Directions

• do not take more than 6 doses in any 24-hour period
• mL = milliliter, tsp = teaspoon

adults and children 12 years of age and over | 5 mL (1 teaspoon) every 4 hours
children under 12 years of age | do not use

Other information

• tamper evident feature: do not use if printed security seal is torn, broken or missing.
• store at controlled room temperature 15-30ºC (59-86ºF) • avoid excessive heat or humidity.

Inactive ingredients

citric acid, flavor, glycerin, methylparaben, propylene glycol, propylparaben, purified water, sodium chloride, sodium citrate, sucralose

Questions or comments?

1-787-767-2072
You may also report serious side effects to this phone number.
Call weekdays from 8:00 am to 4:00 pm AST

Sugar, Alcohol, and Dye FREE

Manufactured for Kramer Novis,
San Juan, PR 00917

www.kramernovis.com

Made in USA with imported ingredients